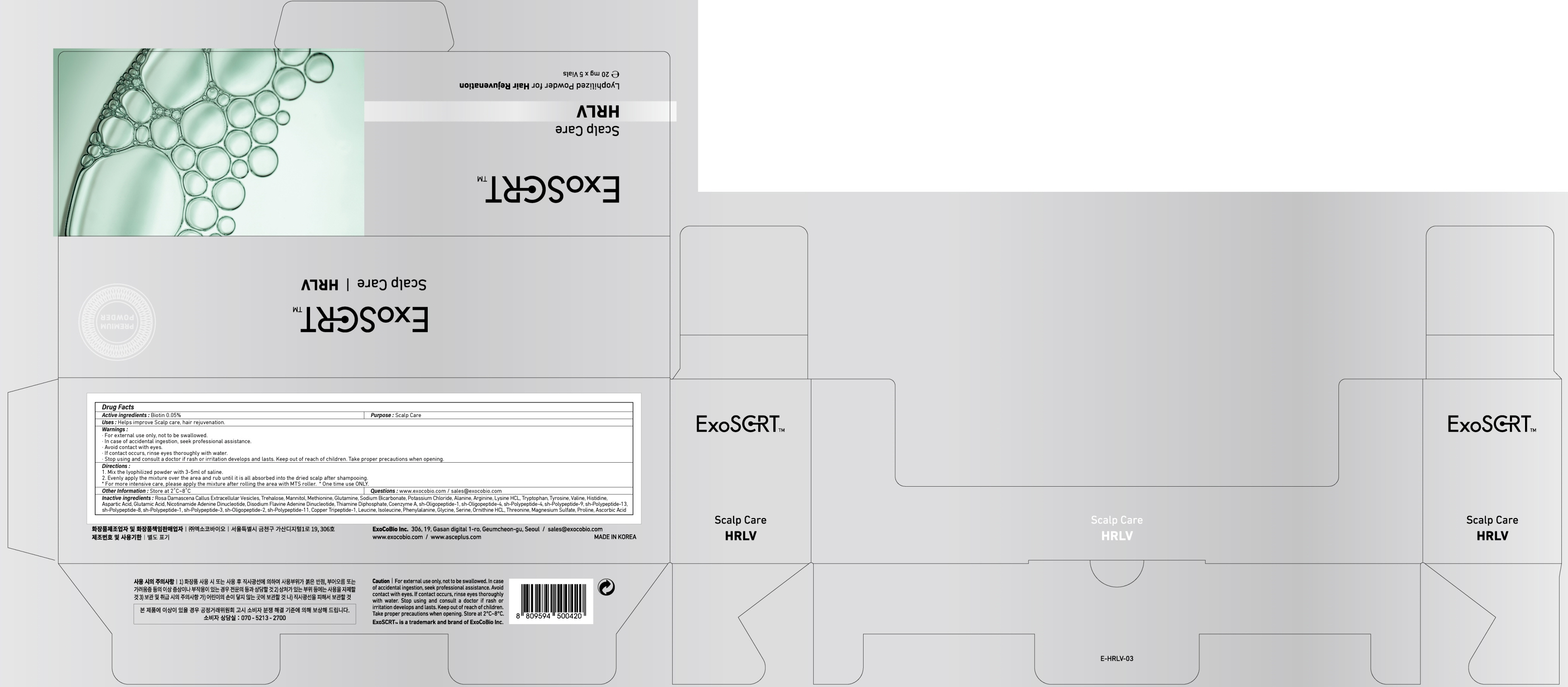 DRUG LABEL: ExoSCRT Scalp Care HRLV
NDC: 72951-130 | Form: POWDER
Manufacturer: Exocobio Inc.
Category: otc | Type: HUMAN OTC DRUG LABEL
Date: 20241209

ACTIVE INGREDIENTS: BIOTIN 0.01 mg/20 mg
INACTIVE INGREDIENTS: TREHALOSE; MANNITOL

ACTIVE INGREDIENT

Biotin 0.05%

INACTIVE INGREDIENTS

Rosa Damascena Callus Extracellular Vesicles, Trehalose, Mannitol, Methionine, Glutamine, Sodium Bicarbonate, Potassium Chloride, Alanine, Arginine, Lysine HCL, Tryptophan, Tyrosine, Valine, Histidine, Aspartic Acid, Glutamic Acid, Nicotinamide Adenine Dinucleotide, Disodium Flavine Adenine Dinucleotide, Thiamine Diphosphate, Coenzyme A, sh-Oligopeptide-1, sh-Oligopeptide-4, sh-Polypeptide-4, sh-Polypeptide-9, sh-Polypeptide-13, sh-Polypeptide-8, sh-Polypeptide-1, sh-Polypeptide-3, sh-Oligopeptide-2, sh-Polypeptide-11, Copper Tripeptide-1, Leucine, Isoleucine, Phenylalanine, Glycine, Serine, Ornithine HCL, Threonine, Magnesium Sulfate, Proline, Ascorbic Acid

PURPOSE

Scalp Care

WARNINGS

For external use only, not to be swallowed.
In case of accidental ingestion, seek professional assistance.
Avoid contact with eyes.
If contact occurs, rinse eyes thoroughly with water.
Stop using and consult a doctor if rash or irritation develops and lasts. Keep out of reach of children. Take proper precautions when opening.

KEEP OUT OF REACH OF CHILDREN

Uses

■ Helps improve Scalp care, hair rejuvenation.

Directions

1. Mix the lyophilized powder with 3-5ml of saline.
2. Evenly apply the mixture over the area and rub until it is all absorbed into the dried scalp after shampooing.
* For more intensive care, please apply the mixture after rolling the area with MTS roller.
* One time use ONLY.

Other Information

Store at 2℃~8℃

Questions

www.exocobio.com / sales@exocobio.com